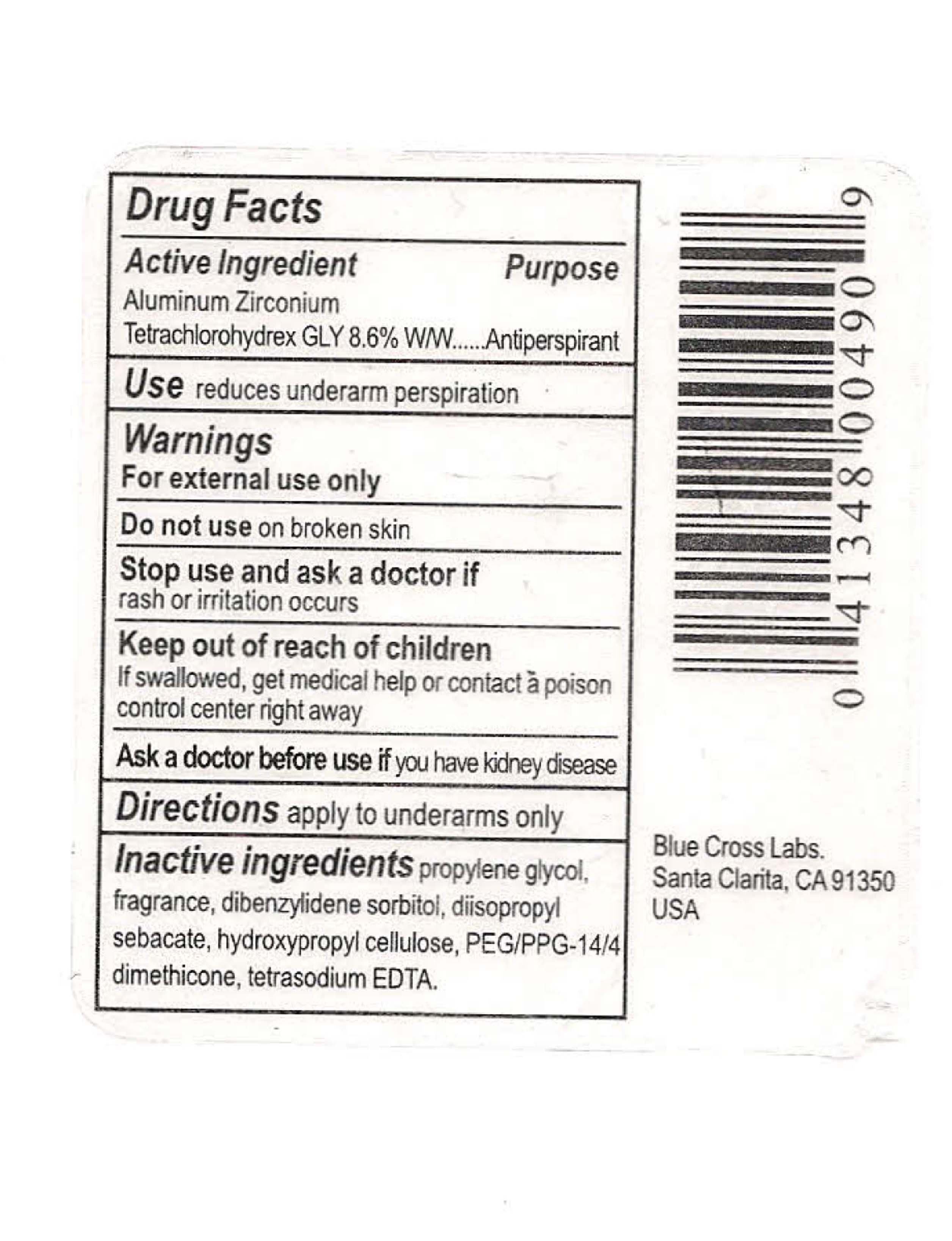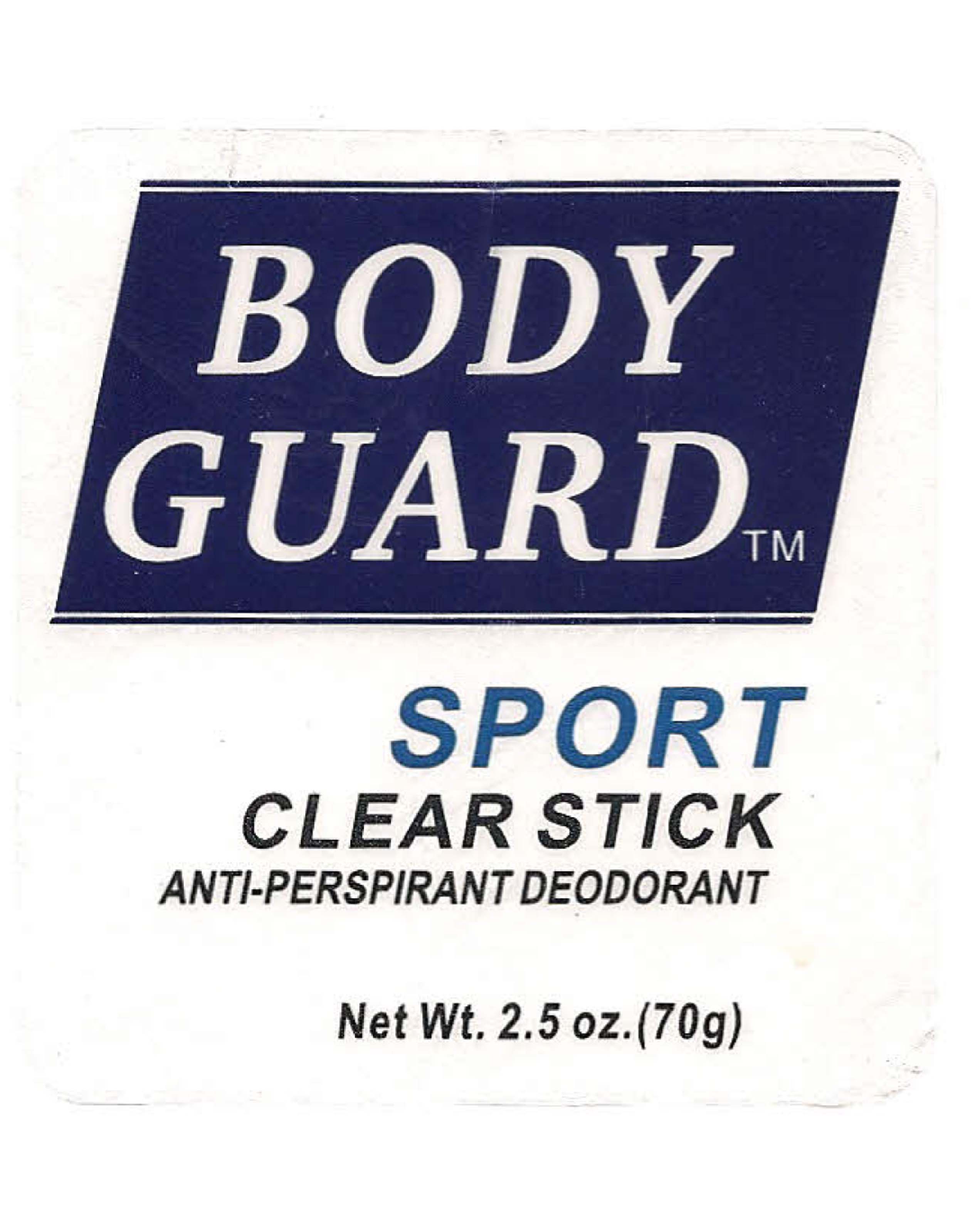 DRUG LABEL: Body Guard
NDC: 22431-328 | Form: STICK
Manufacturer: Blue Cross Laboratories
Category: otc | Type: HUMAN OTC DRUG LABEL
Date: 20121212

ACTIVE INGREDIENTS: ALUMINUM ZIRCONIUM TETRACHLOROHYDREX GLY 70 g/100 g
INACTIVE INGREDIENTS: PROPYLENE GLYCOL; DIISOPROPYL SEBACATE; HYDROXYPROPYL CELLULOSE

Body Guard Sport Clear Stick

Active Ingredient purpose
Aluminum Zirconium Tetrachlorohydrex GLY 8.5% W/W Antiperspirant

PURPOSE

Use reduces underarm perspiration

KEEP OUT OF REACH OF CHILDREN

Enter section text here

Stop use and ask a doctor if rash or irritiation occurs.

Ask a doctor before use if you have kidney disease.
If swallowed, get medical help or contact a poison control center right away.

DOSAGE AND ADMINISTRATION

Directions: apply to underarms only

Inactive ingredients

Propylene glycol, fragrance, dibenzylidene sorbitol, Diisopropyl Sebacate, Hydroxypropyl cellulose, PEG/PPG-14/4 dimethicone, tetrasodium EDTA.

PACKAGE LABEL

Body Guard Sport Clear Stick Anti-perspirant deodorant
Net Wt. 2.5 oz. (70g)